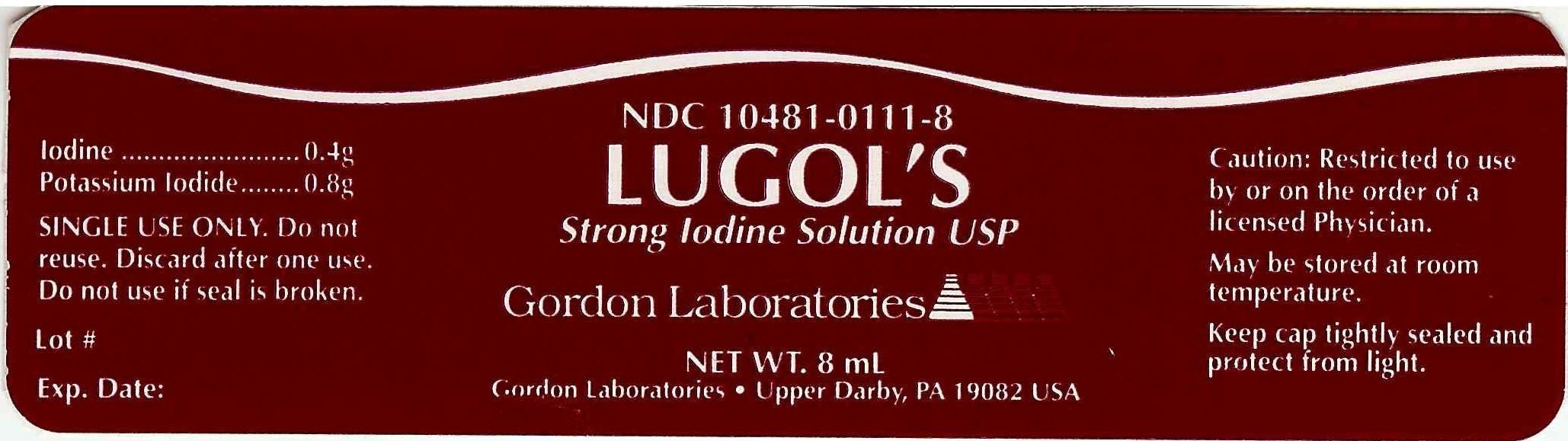 DRUG LABEL: LUGOLS SOLUTION
NDC: 10481-0111 | Form: LIQUID
Manufacturer: Gordon Laboratories
Category: prescription | Type: HUMAN PRESCRIPTION DRUG LABEL
Date: 20100201

ACTIVE INGREDIENTS: IODINE 0.4 g/1 g
INACTIVE INGREDIENTS: POTASSIUM IODIDE; WATER

LUGOLS SOLUTION

DESCRIPTION

Strong Iodine Solution USP a topical anti-infective agent.

HOW SUPPLIED

Applied with a q-tip.

May be stored at room temperature.

WARNINGS AND PRECAUTIONS

Single use only. Do not reuse. Discard after one use. Do not use if seal is broken. Restricted to use by or on the order of a licensed Physician. Keep cap tightly sealed and product from light.